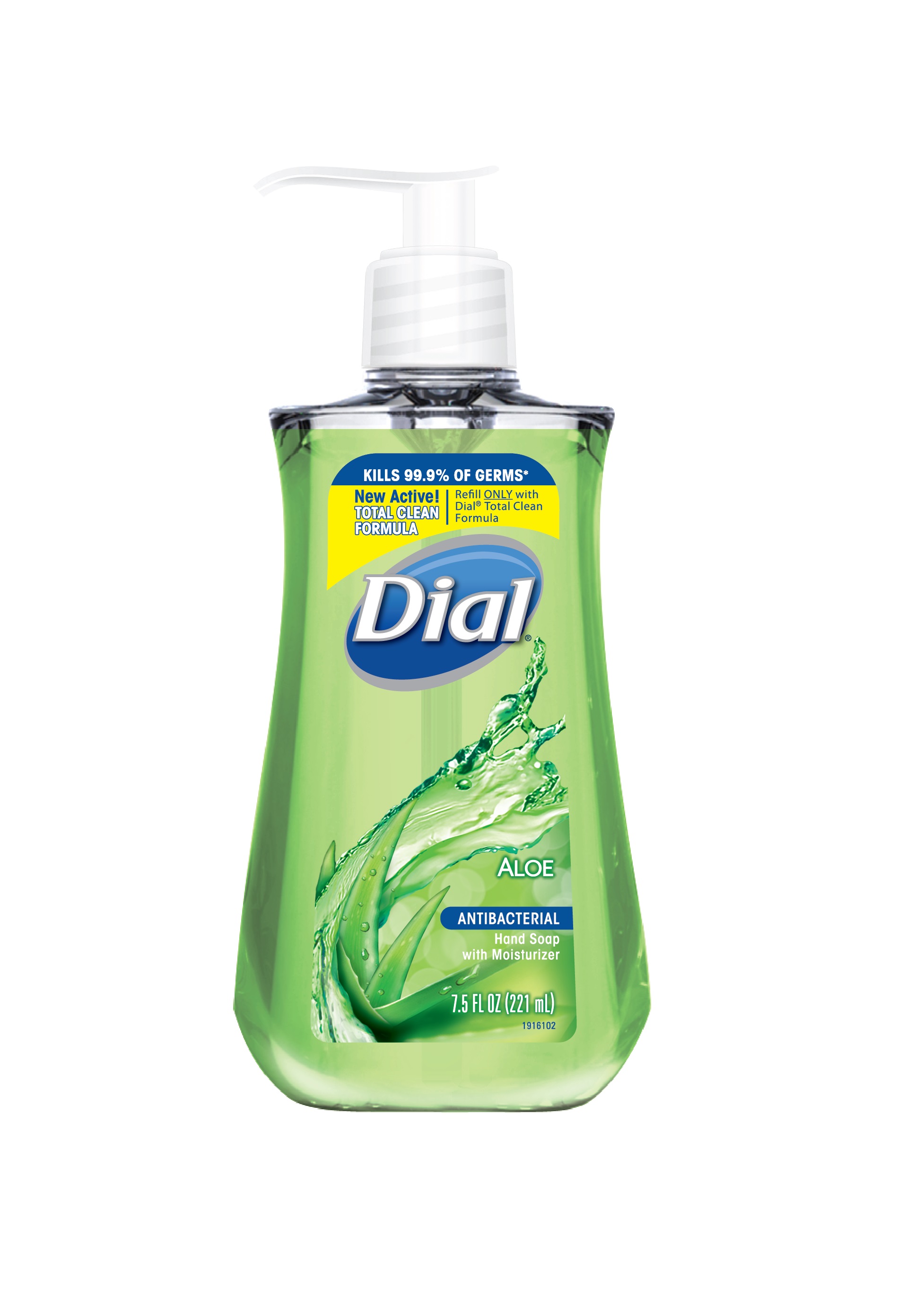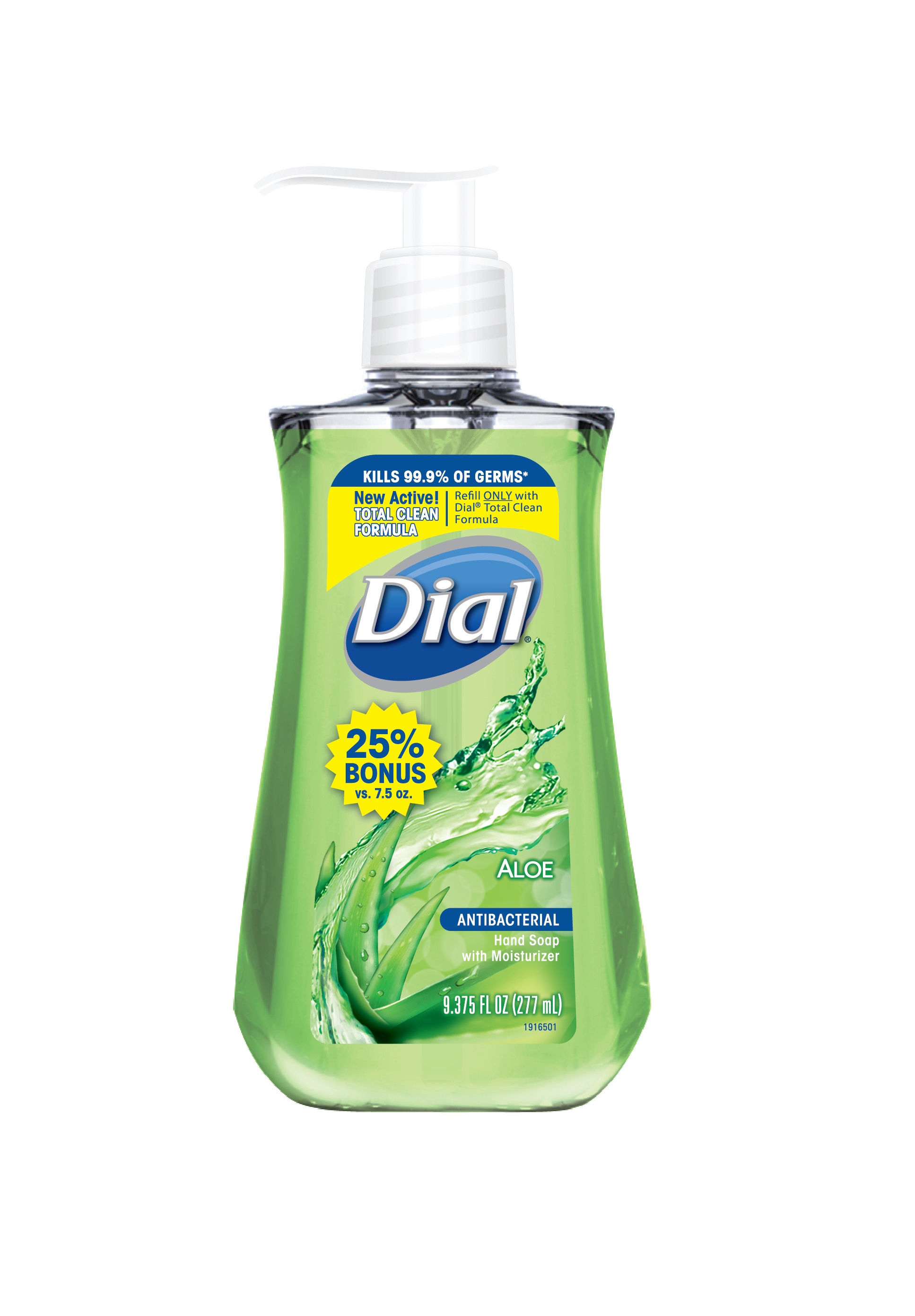 DRUG LABEL: Benzethonium Chloride Solution
NDC: 54340-246 | Form: SOLUTION
Manufacturer: The Dial Corporation, A Henkel Company
Category: otc | Type: HUMAN OTC DRUG LABEL
Date: 20141217

ACTIVE INGREDIENTS: BENZETHONIUM CHLORIDE .1 g/100 mL
INACTIVE INGREDIENTS: PEG-120 METHYL GLUCOSE DIOLEATE; EDETATE SODIUM; COCO MONOETHANOLAMIDE; CITRIC ACID MONOHYDRATE; FD&C YELLOW NO. 5; FD&C BLUE NO. 1; SODIUM CHLORIDE; ALOE VERA LEAF; GLYCOL DISTEARATE; STEARETH-4; LAURAMINE OXIDE; GLYCERIN; CETRIMONIUM CHLORIDE; SODIUM BENZOATE; LAURAMIDOPROPYLAMINE OXIDE

Dial Aloe Antibacterial Hand Soap with Moisturizer

Drug Facts

ACTIVE INGREDIENT

Benzethonium Chloride 0.10%

PURPOSE

Antibacterial

PURPOSE

Uses - For handwashing to decrease bacteria on the skin

WARNINGS

For external use only

When using this product - Avoid contact with eyes. In case of eye contact, flush with water.

Stop use and ask a doctor if irritation and redness develops

Keep out of reach of children. If swallowed, get medical help or contact a Poison Control Center right away.

Directions

- Pump into hands, wet as needed
- lather vigorously for at least 15 seconds
- wash skin, rinse thoroughly and dry

INACTIVE INGREDIENT

Inactive Ingredients: Water, Centrimonium Chloride, Glycerin, Lauramine Oxide, Lauramidopropylamine Oxide, Sodium Chloride, Fragrance, Glycol Distearate, Steareth-4, Aloe Barbadensis Leaf Juice, PEG-120 Methyl Glucose Dioleate, Cocamide MEA, Citric Acid, Sodium Benzoate, Tetrasodium EDTA, Yellow 5, Blue 1

* Encountered in household settings

Questions? 1-800-258-DIAL (3425)

Visit our web site at www.dialsoap.com

© 2014 Distributed by THE DIAL CORPORATION, A (HENKEL) COMPANY

SCOTTSDALE, AZ 85255

MADE IN USA

The distinctive design elements of this package are proprietary and owned by The Dial Corporation, a Henkel Company

DOSAGE AND ADMINISTRATION

Topical liquid

INDICATIONS AND USAGE

For handwashing to decrease bacteria on skin

PACKAGE LABEL

KILLS 99.9% OF GERMS*

New Active!

TOTAL CLEAN FORMULA

Refill ONLY with Dial® Total Clean Formula

Dial Aloe Hand Soap with Moisturizer

Antibacterial

7.5 FL OZ (221 mL)